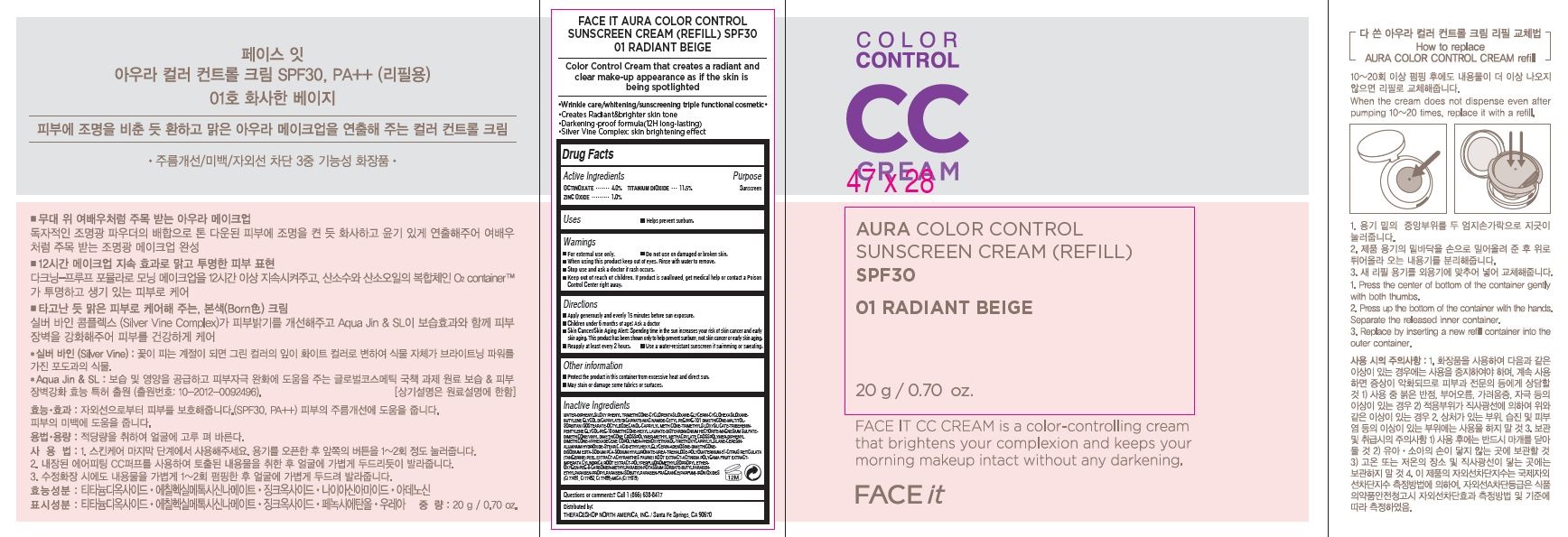 DRUG LABEL: FACE IT AURA COLOR CONTROL SPF30 (REFILL), 01 RADIANT BEIGE
NDC: 51523-659 | Form: CREAM
Manufacturer: THEFACESHOP CO., LTD.
Category: otc | Type: HUMAN OTC DRUG LABEL
Date: 20141120

ACTIVE INGREDIENTS: ZINC OXIDE .2 g/20 g; OCTINOXATE .8 g/20 g; TITANIUM DIOXIDE 2.3 g/20 g
INACTIVE INGREDIENTS: WATER

FACE IT AURA COLOR CONTROL SPF30, PA++(REFILL) 01 RADIANT BEIGE 32800659

Active Ingredients

OCTINOXATE • • • • • • • 4.0%

TITANIUM DIOXIDE • • • 11.5%

ZINC OXIDE • • • • • • • • • 1.0%

Purpose

Sunscreen

Sunscreen

Sunscreen

Uses

Helps prevent sunburn.

Warnings

For external use only. Do not use on damaged or broken skin.

When using this product keep out of eyes. Rinse with water to remove.

Stop use and ask a doctor if rash occurs.

Keep out of reach of children. If product is swallowed, get medical help or contact a Poison

Control Center right away.

Directions

Apply generously and evenly 15 minutes before sun exposure.

Children under 6 months of age: Ask a doctor

Skin Cancer/Skin Aging Alert: Spending time in the sun increases your risk of skin cancer and early

skin aging. This product has been shown only to help prevent sunburn, not skin cancer or early skin aging.

Reapply at least every 2 hours. Use a water-resistant sunscreen if swimming or sweating

Other information

Protect the product in this container from excessive heat and direct sun.

May stain or damage some fabrics or surfaces.

Inactive Ingredients

WATER•DIPHENYLSILOXY PHENYL TRIMETHICONE•CYCLOPENTASILOXANE•GLYCERIN•CYCLOHEXASILOXANE•

BUTYLENE GLYCOL DICAPRYLATE/DICAPRATE•NIACINAMIDE•CETYL PEG/PPG-10/1 DIMETHICONE•MALTITOL•

SORBITAN ISOSTEARATE•OCTYLDODECANOL•CAPRYLYL METHICONE•TRIMETHYLSILOXYSILICATE•TRIBEHENIN•

PENTYLENE GLYCOL•PEG-10 DIMETHICONE•HEXYL LAURATE•DISTEARDIMONIUM HECTORITE•MAGNESIUM SULFATE•

DIMETHICONE/VINYL DIMETHICONE CROSSPOLYMER•METHYL METHACRYLATE CROSSPOLYMER•DIPHENYL

DIMETHICONE•VP/HEXADECENE COPOLYMER•PHENOXYETHANOL•TRIETHOXYCAPRYLYLSILANE•CERESIN•

ALUMINUM HYDROXIDE•STEARIC ACID•ETHYLHEXYLGLYCERIN•ADENOSINE•DIMETHICONE•

DISODIUM EDTA•SODIUM PCA•SODIUM HYALURONATE•UREA•TREHALOSE•POLYQUATERNIUM-51•CITRUS RETICULATA

(TANGERINE) PEEL EXTRACT•ACHYRANTHES FAURIEI ROOT EXTRACT•ACTINIDIA POLYGAMA FRUIT EXTRACT•

IMPERATA CYLINDRICA ROOT EXTRACT•POLYPERFLUOROMETHYLISOPROPYL ETHER•

OXYGEN•PEG-8•CARBOMER•METHYLPARABEN•POTASSIUM SORBATE•BUTYLPARABEN•

ETHYLPARABEN•PROPYLPARABEN•ISOBUTYLPARABEN•FRAGRANCE(PARFUM)•IRON OXIDES

(CI 77491, CI 77492, CI 77499)•MICA (CI 77019)

Questions or comments? Call 1 (866) 638-8417

Distributed by:

THEFACESHOP NORTH AMERICA, INC. / Santa Fe Springs, CA 90670

PACKAGE LABEL

FACE IT AURA COLOR CONTROL CREAM SPF30 (REFILL) 01 RADIANT BEIGE